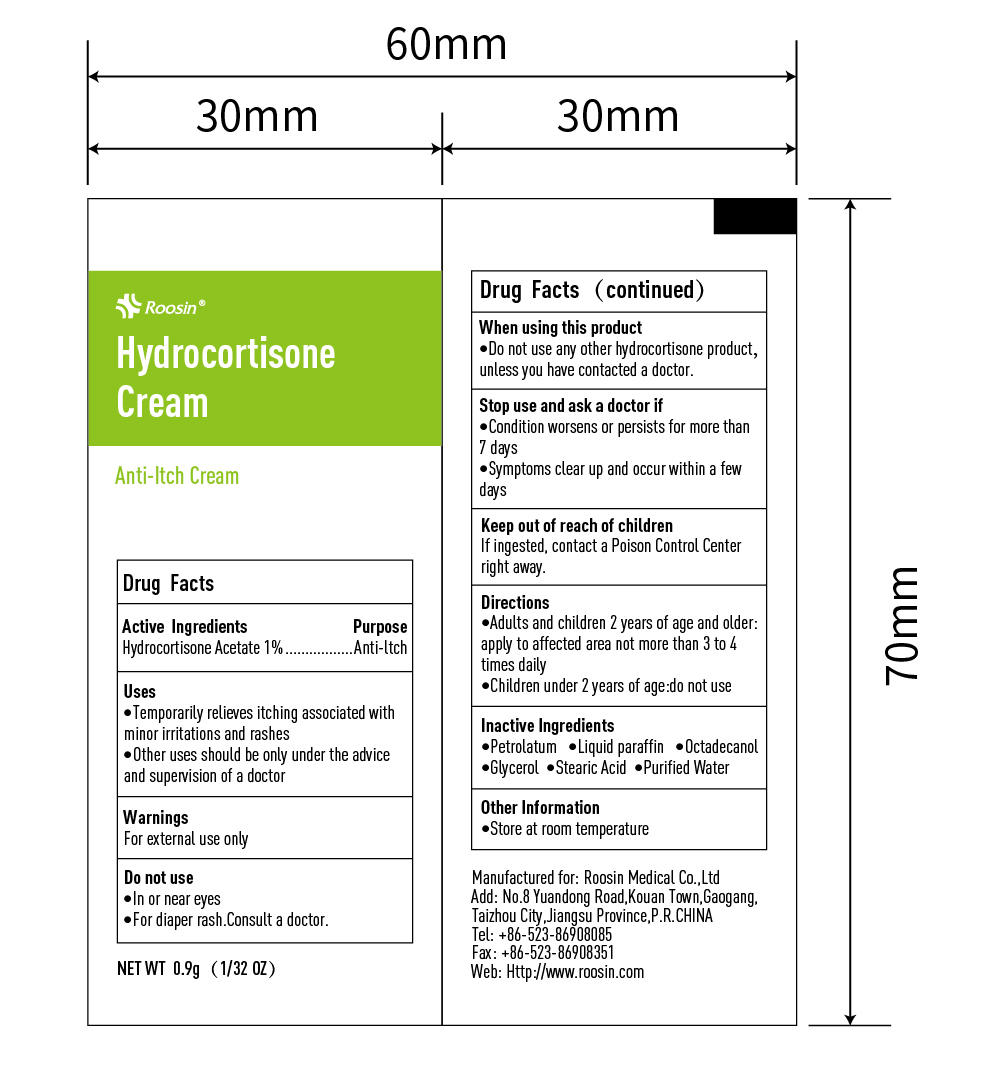 DRUG LABEL: Roosin
NDC: 81552-003 | Form: CREAM
Manufacturer: ROOSIN MEDICAL CO., LTD
Category: otc | Type: HUMAN OTC DRUG LABEL
Date: 20211215

ACTIVE INGREDIENTS: HYDROCORTISONE ACETATE 1 g/100 g
INACTIVE INGREDIENTS: PETROLATUM; PARAFFIN; OCTADECANOL (MIXTURE OF ISOMERS); WATER; STEARIC ACID; GLYCEROL FORMAL

81552-003 Hydrocortisone Cream

Active Ingredient

Hydrocortisone 1%

Purpose

Anti-Itch

Use

Temporary relieves itching associated with minor irritations and rashes

Other uses should be only under the advice and supervision of a doctor

WARNINGS

For external use only

Do not use

- In or near eyes
- For diaper rash, consult a doctor

When using this product

- Do not use any other hydrocortisone products unless you have contacted a doctor

Stop use and ask a doctor if

Condition worsens or persists for more than 7 days

Symptoms clear up and occur within a few days

Keep out of reach of children. If ingested, get medical help or contact a poison control center right away

Directions

Adults and children two years of age and older: Apply to affected area not more than 3-4 timesdaily

Children under 2 years of age: Do not use

Inactive ingredients

Petrolactum, Liquid Paraffin, Octadecanol, Glycerol, Stearic Acid, Purified Water

Other Information

Store at room temperature